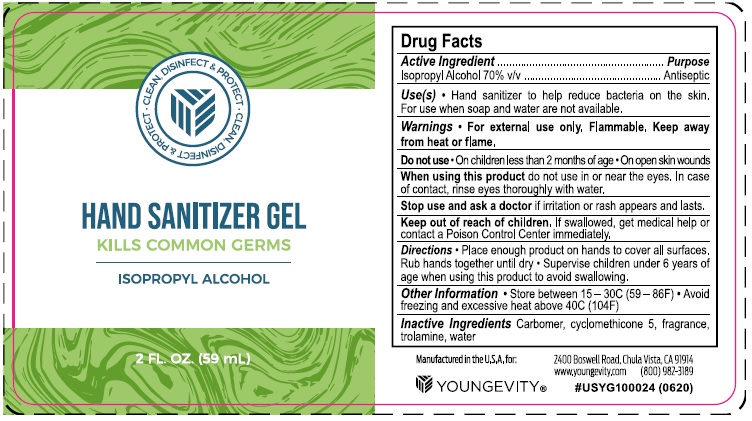 DRUG LABEL: Hand Sanitizer
NDC: 80986-102 | Form: GEL
Manufacturer: Youngevity International Inc.
Category: otc | Type: HUMAN OTC DRUG LABEL
Date: 20201118

ACTIVE INGREDIENTS: ISOPROPYL ALCOHOL 71.7 mL/100 mL
INACTIVE INGREDIENTS: CYCLOMETHICONE 5 1.08 g/100 mL; CARBOMER HOMOPOLYMER, UNSPECIFIED TYPE 0.125 g/100 mL; WATER; TROLAMINE 0.03 g/100 mL

Youngevity Hand Sanitizer

Active Ingredient(s)

Isopropyl Alcohol 70% v/v. Purpose: Antiseptic

Purpose

Antiseptic, Hand Sanitizer

Use

Hand Sanitizer to help reduce bacteria that potentially can cause disease. For use when soap and water are not available.

Warnings

For external use only. Flammable. Keep away from heat or flame

Do not use

- in children less than 2 months of age
- on open skin wounds

When using this product do not use in or near the eyes. In case of contact, rinse eyes thoroughly with water.

Stop use and ask a doctor if irritation or rash occurs. These may be signs of a serious condition.

Keep out of reach of children. If swallowed, get medical help or contact a Poison Control Center immediately.

Directions

- Place enough product on hands to cover all surfaces. Rub hands together until dry.
- Supervise children under 6 years of age when using this product to avoid swallowing.

Other information

- Store between 15-30C (59-86F)
- Avoid freezing and excessive heat above 40C (104F)

Inactive ingredients

Carbomer, cyclomethicone 5, fragrance, trolamine, water

Package Label - Principal Display Panel

59 ml NDC: 80986-102-02